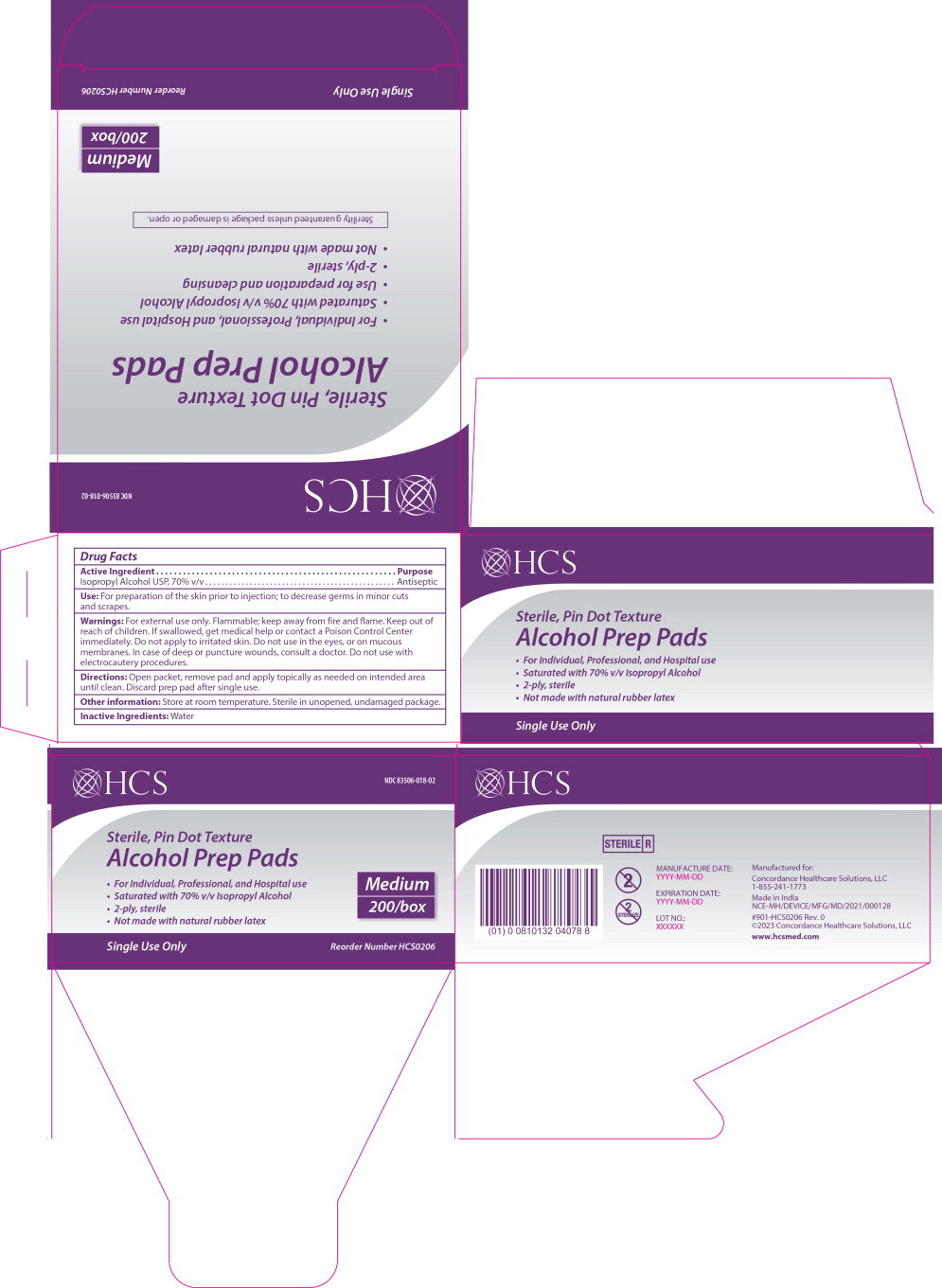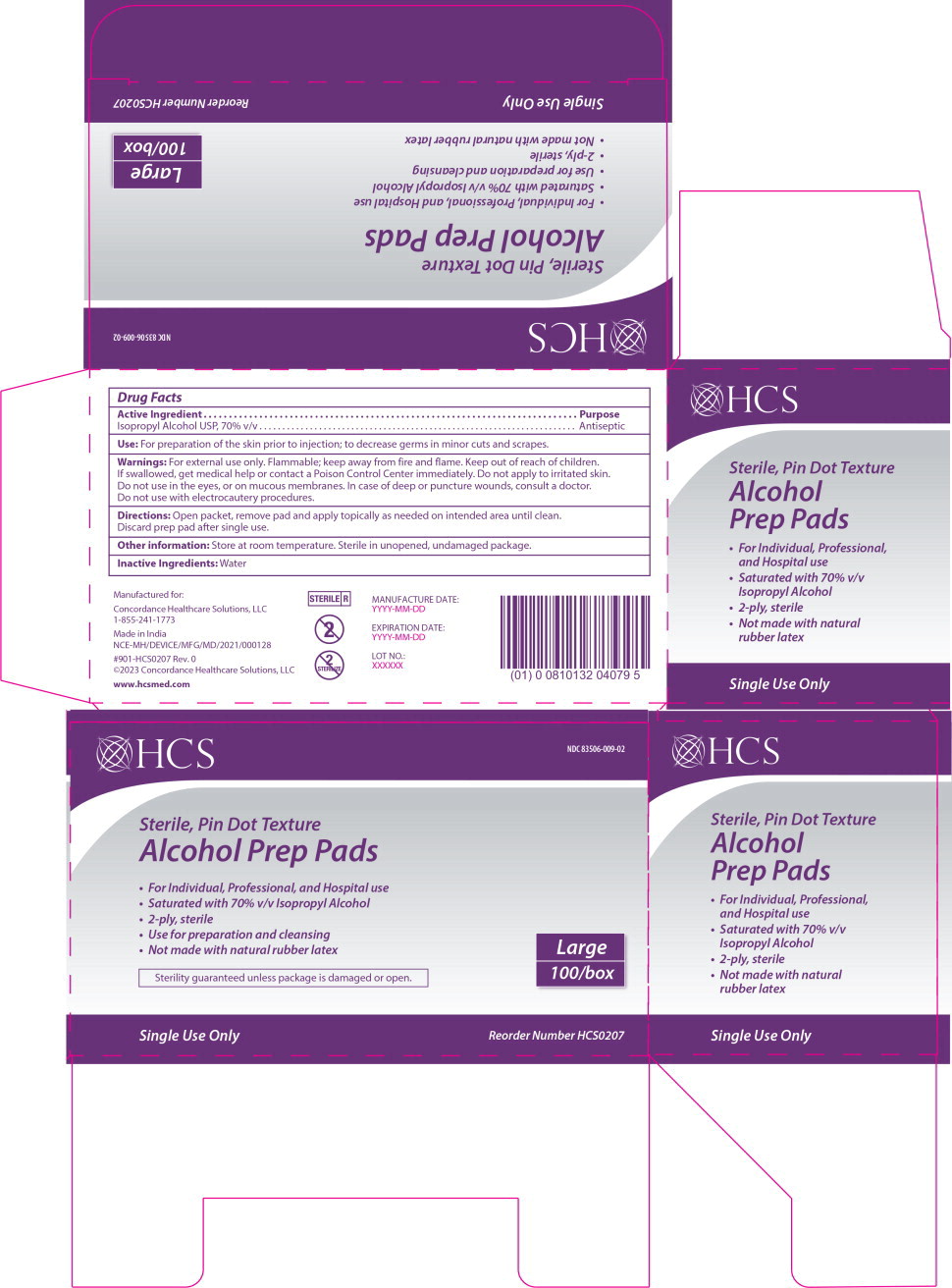 DRUG LABEL: HCS Alcohol Prep Pad Medium
NDC: 83506-018 | Form: SWAB
Manufacturer: Concordance Healthcare Solutions, LLC.
Category: otc | Type: HUMAN OTC DRUG LABEL
Date: 20260112

ACTIVE INGREDIENTS: Isopropyl Alcohol 70 mL/100 mL
INACTIVE INGREDIENTS: Water

Drug Facts

Active Ingredient

Isopropyl Alcohol USP, 70% v/v

Purpose

Antiseptic

Use:

For preparation of the skin prior to injection; to decrease germs in minor cuts and scrapes.

Warnings:

For external use only. Flammable; keep away from fire and flame.

Keep out of reach of children. If swallowed, get medical help or contact a Poison Control Center immediately.

DO NOT USE

Do not apply to irritated skin. Do not use in the eyes, or on mucous membranes. In case of deep or puncture wounds, consult a doctor. Do not use with electrocautery procedures.

Directions:

Open packet, remove pad and apply topically as needed on intended area until clean. Discard prep pad after single use.

Other information:

Store at room temperature. Sterile in unopened, undamaged package.

Inactive Ingredients:

Water

Principal Display Panel – Large 100 count Box Label

HCS

NDC 83506-009-02

Sterile, Pin Dot Texture

Alcohol Prep Pads

- For Individual, Professional, and Hospital use
- Saturated with 70% v/v Isopropyl Alcohol
- 2-ply, sterile
- Use for preparation and cleansing
- Not made with natural rubber latex

Sterility guaranteed unless package is damaged or open.

Large

100/box

Single Use Only

Reorder Number HCS0207

Principal Display Panel – Medium 200 count Box Label

HCS

NDC 83506-018-02

Sterile, Pin Dot Texture

Alcohol Prep Pads

- For Individual, Professional, and Hospital use
- Saturated with 70% v/v Isopropyl Alcohol
- 2-ply, sterile
- Not made with natural rubber latex

Medium

200/box

Single Use Only

Reorder Number HCS0206